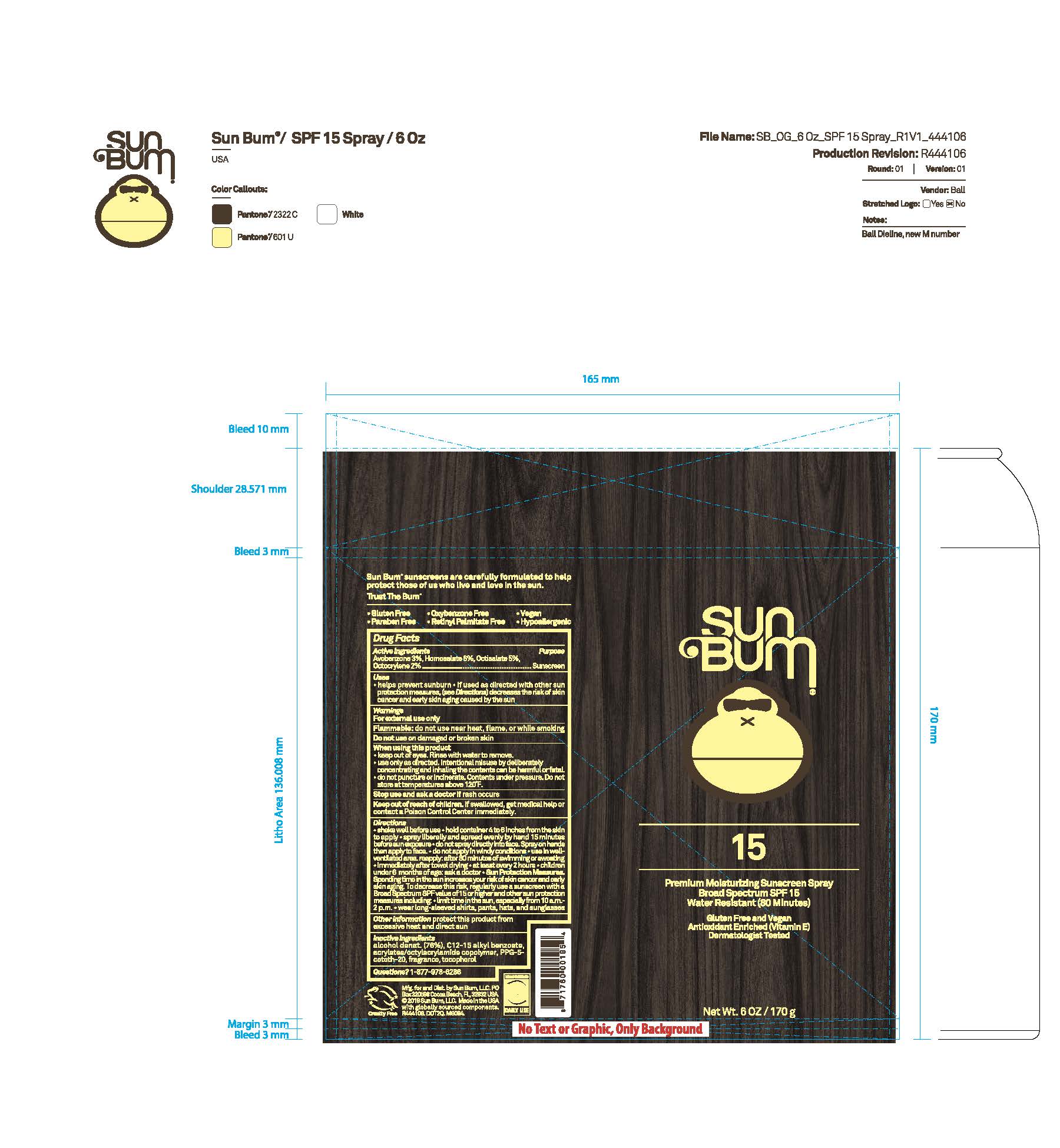 DRUG LABEL: Sun Bum 15 Premium Moisturizing Sunscreen
NDC: 69039-807 | Form: SPRAY
Manufacturer: Sun Bum, LLC
Category: otc | Type: HUMAN OTC DRUG LABEL
Date: 20250828

ACTIVE INGREDIENTS: OCTISALATE 50 mg/1 g; OCTOCRYLENE 20 mg/1 g; HOMOSALATE 60 mg/1 g; AVOBENZONE 30 mg/1 g
INACTIVE INGREDIENTS: ALCOHOL; C12-15 ALKYL BENZOATE; ACRYLATES/OCTYLACRYLAMIDE COPOLYMER (40000 MW); PPG-5-CETETH-20; TOCOPHEROL

Sun Bum 15 Premium Moisturizing Sunscreen

Active Ingredients

AVOBENZONE 3%, HOMOSALATE 6%, OCTISALATE 5%, OCTOCRYLENE 2%

Purpose

Sunscreen

Uses

• helps prevent sunburn • if used as directed with other sun protection measures, (see Directions) decreases the risk of skin cancer and early skin aging caused by the sun

Warnings

For external use only

Flammable: do not use near hear, flame, or while smoking

Do not use on damaged or broken skin

When using this product

• keep out of eyes. Rinse with water to remove.

• use only as directd. Intentional misuse by deliberately concentrating and inhaling the contents can be harmful or fatal.

• do not puncture or incinerate. Contents under pressure. Do not store at temperatures above 120°F.

Stop use and ask a doctor if rash occurs

Keep out of reach of children. If swallowed, get medical help or contact a Poison Control Center immediately.

Warnings

Keep Out Of Reach Of Children

Directions

• shake well before use

• hold container 4 to 6 inches from the skin to apply

• spray liberally and spread evenly by hand 15 minutes before sun exposure

• do not spray directly onto face. Spray on hands then apply to face.

• do not apply in windy conditions

• use in a well-ventilated area

•Avoid inhaling or exposing others to spray

• reapply: after 80 minutes of swimming or sweating

• immediately after towel drying

• at least every 2 hours

• children under 6 months of age: ask a doctor

• Sun Protection Measures. Spending time in the sun increases your risk of skin cancer and early skin aging. To decrease this risk, regularly use a sunscreen with a Broad Spectrum SPF value of 15 or higher and other sun protection measures including:

• limit time in the sun, especially from 10 a.m.- 2 p.m.

Directions

• shake well before use

• hold container 4 to 6 inches from the skin to apply

• spray liberally and spread evenly by hand 15 minutes before sun exposure

• do not spray directly onto face. Spray on hands then apply to face.

• do not apply in windy conditions

• use in a well-ventilated area

•Avoid inhaling or exposing others to spray

Other Information

protect this product from excessive heat and direct sun

Inactive Ingredients

alcohol denat. (76%), C12-15 alkyl benzoate, acrylates/octylacrylamide copolymer, PPG-5-ceteth-20, fragrance, tocopherol

Questions?

1-877-978-6286